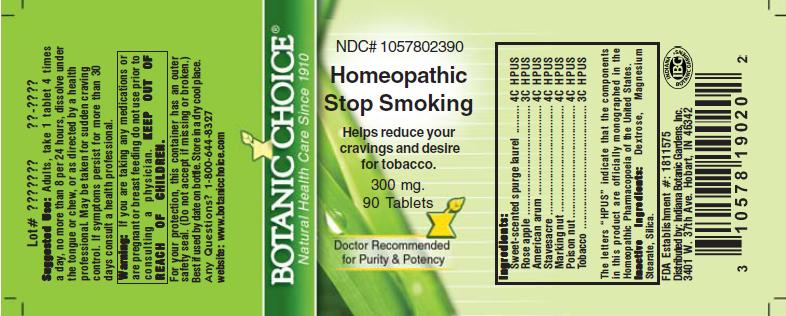 DRUG LABEL: Homeopathic Stop Smoking  Formula
NDC: 10578-023 | Form: TABLET
Manufacturer: Indiana Botanic Gardens
Category: homeopathic | Type: HUMAN OTC DRUG LABEL
Date: 20110325

ACTIVE INGREDIENTS: DAPHNE ODORA BARK 4 [hp_C]/1 1; SYZYGIUM JAMBOS SEED 3 [hp_C]/1 1; DIEFFENBACHIA SEGUINE 4 [hp_C]/1 1; DELPHINIUM STAPHISAGRIA SEED 4 [hp_C]/1 1; SEMECARPUS ANACARDIUM JUICE 4 [hp_C]/1 1; STRYCHNOS NUX-VOMICA SEED 4 [hp_C]/1 1; TOBACCO LEAF 3 [hp_C]/1 1
INACTIVE INGREDIENTS: DEXTROSE; MAGNESIUM STEARATE ; SILICON DIOXIDE 

Homeopathic Stop Smoking Formula

ACTIVE INGREDIENT

I n g r e d i e n t s :

Sweet-scented spurge laurel............................ 4C HPUS
Rose apple....................... 3C HPUS
American arum.................... 4C HPUS
Stavesacre.............................. 4C HPUS
Marking nut.................. 4C HPUS
Poison nut............................... 4C HPUS
Tobacco................................. 3C HPUS

The letters “HPUS” indicate that the components in
this product are officially monographed in the
Homeopathic Pharmacopoeia of the United States.

PURPOSE

Helps reduce your cravings and desire for tobacco

KEEP OUT OF
REACH OF CHILDREN.

INDICATIONS AND USAGE

Helps reduce your cravings and desire for tobacco

WARNINGS

Warning: If you are taking any medications or
are pregnant or breast feeding do not use prior to
consulting a physician.

DOSAGE AND ADMINISTRATION

Suggested Use: Adults, take 1 tablet 4 times a day, no more than 8 per
24 hours, dissolve under tongue or
chew, or as directed by a health care
professional. My be taken for sudden craving control.
If symptoms persist for more than 30 days consult a
health professional.

Inactive Ingredients: Dextrose, Magnesium
Stearate, Silica.

PACKAGE LABEL

NDC# 1057802390

Homeopathic Stop Smoking Formula

Helps reduce your cravings and desire for tobacco

300 mg.
90 Tablets

USER SAFETY WARNINGS

For your protection, this container has an outer
safety seal. (Do not accept if missing or broken.)
Best if used by date on bottle. Store in a dry cool place.
Any Questions? 1-800-644-8327
website: www.botanicchoice.com

FDA Establishment #: 1811575

Distributed by: Indiana Botanic Gardens, Inc.
3401 W. 37th Ave. Hobart, IN 46342